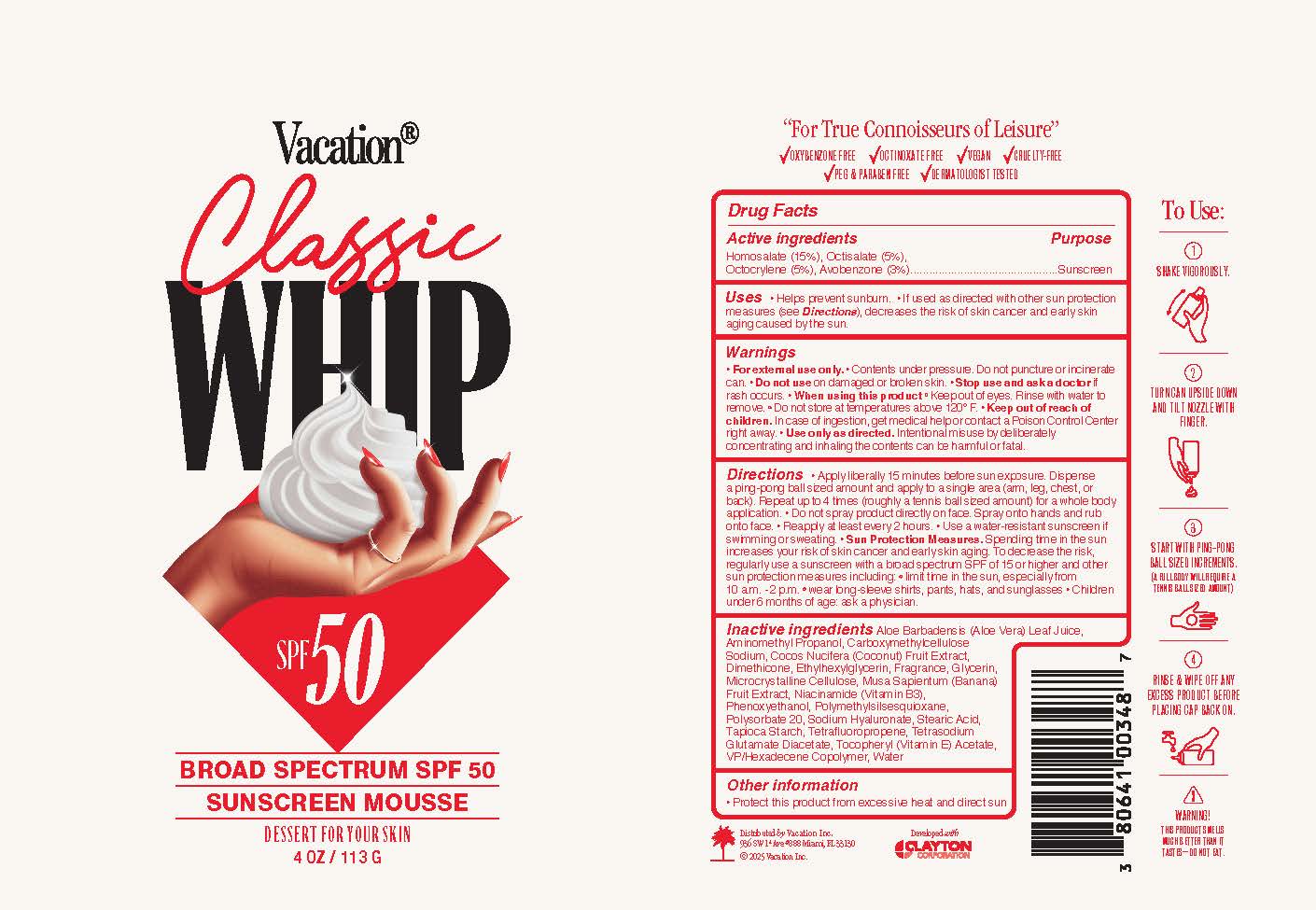 DRUG LABEL: Vacation Classic Whip SPF 50
NDC: 80641-021 | Form: AEROSOL, FOAM
Manufacturer: Vacation Inc.
Category: otc | Type: HUMAN OTC DRUG LABEL
Date: 20250605

ACTIVE INGREDIENTS: OCTISALATE 0.05 g/1 g; HOMOSALATE 0.15 g/1 g; OCTOCRYLENE 0.05 g/1 g; AVOBENZONE 0.03 g/1 g
INACTIVE INGREDIENTS: POLYMETHYLSILSESQUIOXANE (11 MICRONS); AMINOMETHYLPROPANOL; GLYCERIN; NIACINAMIDE; STEARIC ACID; TAPIOCA STARCH; TETRASODIUM GLUTAMATE DIACETATE; PHENOXYETHANOL; ALPHA-TOCOPHEROL ACETATE; VINYLPYRROLIDONE/HEXADECENE COPOLYMER; DIMETHICONE; BANANA; WATER; ALOE BARBADENSIS LEAF JUICE; COCOS NUCIFERA (COCONUT) FRUIT; ETHYLHEXYLGLYCERIN; 1,3,3,3-TETRAFLUOROPROPENE, (1E)-; SODIUM HYALURONATE; POLYSORBATE 20; MICROCRYSTALLINE CELLULOSE; CARBOXYMETHYLCELLULOSE SODIUM

Vacation Classic Whip SPF 50 Sunscreen Mouse

Active ingredients

Homosalate 15%, Octisalate 5%, Octocrylene 5%, Avobenzone 3%

Purpose

Sunscreen

Uses

- helps prevent sunburn
- if used as directed with other sun protection measures (see Directions), decreases the risk of skin cancer and early skin aging caused by the sun

Warnings

- For external use only
- Contents under pressure. Do not puncture or incinerae can
- Do not store at temperatures above 120 F
- Use only as directed. Intentional misuse by deliberately concentrating and inhaling the contents can be harmful or fatal.

Do not use

on damaged or broken skin

Stop use and ask a doctor

if rash occurs

When using this product

Keep out of eyes. Rinse with water to remove.

Keep out of reach of children

In case of ingestion, get medical help or contact a Poison Control Center right away.

Directions

- Apply liberally 15 minutes before sun exposure
- Dispense a ping-pong ball sized amount and apply to a single area (arm, leg, chest, or back). Repeat up to 4 times (roughly a tennis ball sizes amount) for a whole body application
- Do not spray product directly on face. Spray onto hands and rub onto face.
- Reapply at least every 2 hours.
- Use a water resistant sunscreen if swimming or sweating
- Sun Protection Measures: Spending time in the sun increases your risk of skin cancer and early skin aging. To decrease the risk, regularly use a sunscreen with a broad spectrum SPF of 15 or higher and other sun protection measures including:
- Limit time in the sun, especially from 10 a.m. - 2 p.m.
- Wear long-sleeve shirts, pants, hats, and sunglasses
- Children under 6 months of age: ask a physician

Inactive ingredients

Aloe Barbandensis (Aloe Vera) Leaf Juice, Aminomethyl Propanol, Carboxymethylcellulose Sodium, Cocos Nucifera (Coconut) Fruit Extract, Dimethicone, Ethylhexylglycerin, Fragrance, Glycerin, Microcrystalline Cellulose, Musa Sapientum (Banana) Fruit Extract, Niacinamide (Vitamin B3), Phenoxyethanol, Polymethylsilsesquioxane, Polysorbate 20, Sodium Hyaluronate, Stearic Acid, Tapioca Starch, Tetrafluoropropene, Tetrasodium Glutamate Diacetate, Tocopheryl (Vitamin E) Acetate, VP/Hexadecene Copolymer, Water

Other information

Protect this product from excessive heat and direct sun